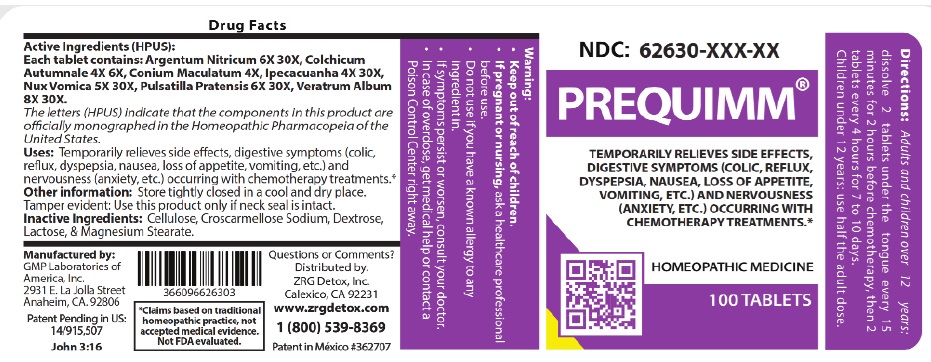 DRUG LABEL: PreQuimm
NDC: 62630-003 | Form: TABLET
Manufacturer: ZRG Detox, Inc.
Category: homeopathic | Type: HUMAN OTC DRUG LABEL
Date: 20251027

ACTIVE INGREDIENTS: SILVER NITRATE 6 [hp_X]/1 1; COLCHICUM AUTUMNALE BULB 4 [hp_X]/1 1; CONIUM MACULATUM FLOWERING TOP 4 [hp_X]/1 1; IPECAC 4 [hp_X]/1 1; STRYCHNOS NUX-VOMICA SEED 5 [hp_X]/1 1; PULSATILLA PRATENSIS WHOLE 6 [hp_X]/1 1; VERATRUM ALBUM ROOT 8 [hp_X]/1 1
INACTIVE INGREDIENTS: POWDERED CELLULOSE; CROSCARMELLOSE SODIUM; DEXTROSE, UNSPECIFIED FORM; LACTOSE, UNSPECIFIED FORM; MAGNESIUM STEARATE

DRUG FACTS:

ACTIVE INGREDIENTS:

Each tablet contain Argentum Nitricum 6X, 30X, Colchicum Autumnale 4X, 6X, Conium Maculatum 4X, Ipecacuanha 4X, 30X, Nux Vomica 5X, 30X, Pulsatilla Pratensis 6X, 30X, Veratrum Album 8X, 30X

PURPOSE:

Temporarily relieves side effects, digestive symptoms (colic, reflux, dyspepsia, nausea, loss of appetite, vomiting, etc.) and nervousness (anxiety, etc.) occurring with chemotherapy treatments.

WARNINGS:

If pregnant or nursing,ask a healthcare professional before use.

Do not use if you have a known allergy to any ingredient in.

If symptoms persist or worsen, consult your doctor.

In case of overdose, get medical help or contact a Poison Control Center right away.

DIRECTIONS:

Adults and children over 12 years:

dissolve 2 tablets under the tongue every 15 minutes for 2 hours before chemotherapy,

then 2 tablets every 4 hours for 7 to 10 days.

Children under 12 years: use half the adult dose.

OTHER INFORMATION:

Store tightly closed in a cool and dry place.

Tamper evident: Use this product only if neck seal is intact.

INDICATIONS:

Temporarily relieves side effects, digestive symptoms (colic, reflux, dyspepsia, nausea, loss of appetite, vomiting, etc.) and nervousness (anxiety, etc.) occurring with chemotherapy treatments.

INACTIVE INGREDIENTS:

Cellulose, Croscarmellose Sodium, Dextrose, Lactose & Magnesium Stearate

QUESTIONS:

Distributed by.

ZRG Detox, Inc.

Calexico, CA 92231

www.zrgdetox.com

1 (800) 539-8369